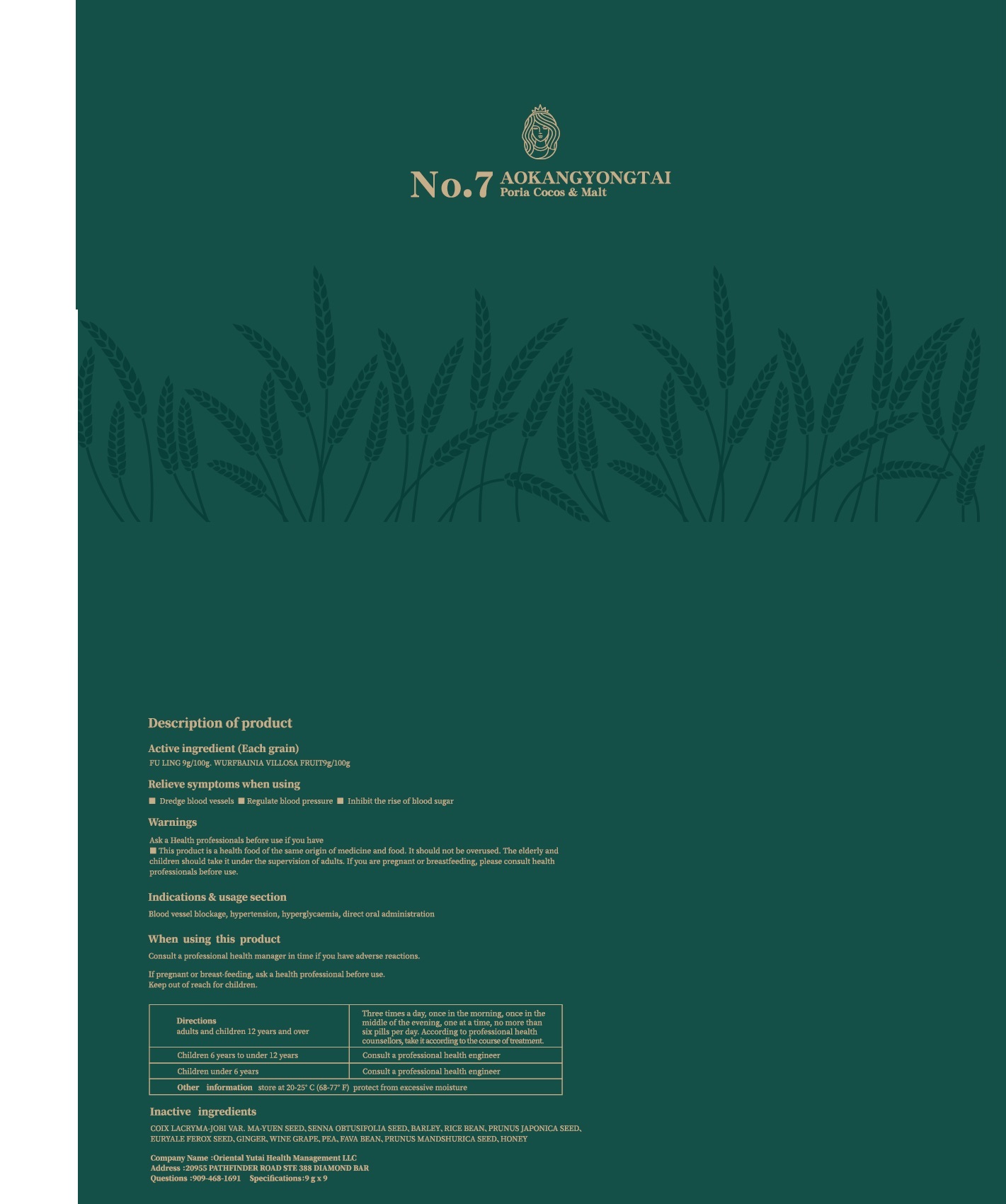 DRUG LABEL: FU LING CAKE
NDC: 83494-002 | Form: OINTMENT
Manufacturer: Oriental Yutai Health Management LLC
Category: homeopathic | Type: HUMAN OTC DRUG LABEL
Date: 20230601

ACTIVE INGREDIENTS: FU LING 9 g/100 g; WURFBAINIA VILLOSA FRUIT 9 g/100 g
INACTIVE INGREDIENTS: GINGER; WINE GRAPE; PRUNUS MANDSHURICA SEED; SENNA OBTUSIFOLIA SEED; BARLEY; RICE BEAN; PEA; COIX LACRYMA-JOBI VAR. MA-YUEN SEED; EURYALE FEROX SEED; PRUNUS JAPONICA SEED; FAVA BEAN; HONEY

Active ingredients

FU LING 9% w/w.

WURFBAINIA VILLOSA FRUIT 9% w/w

Relieve symptoms when using

■ Dredge blood vessels ■ Regulate blood pressure ■ Inhibit the rise of blood sugar

Indications & usage section

Blood vessel blockage, hypertension, hyperglycaemia, direct oral administration

Warnings

Ask a Health professionals before use if you have

■This product is a health food of the same origin of medicine and food. It should not be overused. The elderly and children should take it under the supervision of adults. If you are pregnant or breastfeeding, please consult health professionals before use.

Keep out of reach for children.

When using this product

Consult a professional health manager in time if you have adverse reactions.
If pregnant or breast-feeding, ask a health professional before use.

Directions

adults and children 12 years and over

three times a day, once in the morning, once in the middle of the evening, one at a time, no more than six pills per day. According to professional health counsellors, take it according to the course of treatment.

children 6 years to under 12 years

Consult a professional health engineer

children under 6 years

Consult a professional health engineer

Inactive ingredients

COIX LACRYMA-JOBI VAR. MA-YUEN SEED、SENNA OBTUSIFOLIA SEED、BARLEY、RICE BEAN、PRUNUS JAPONICA SEED、EURYALE FEROX SEED、GINGER、WINE GRAPE、PEA、FAVA BEAN、PRUNUS